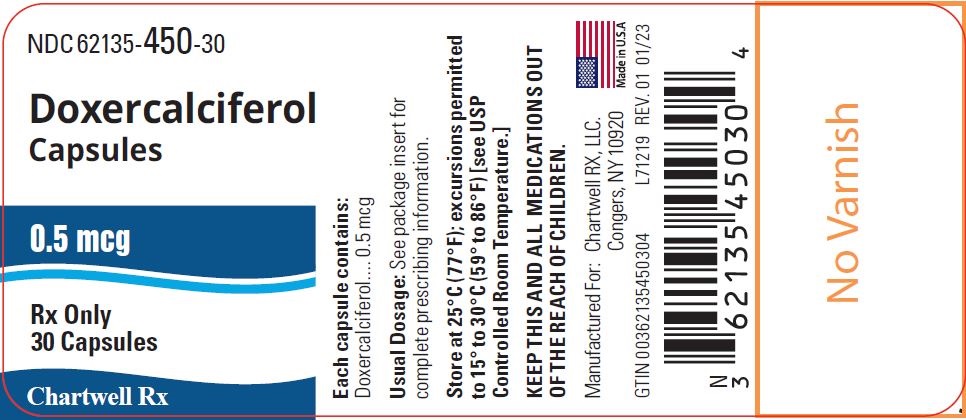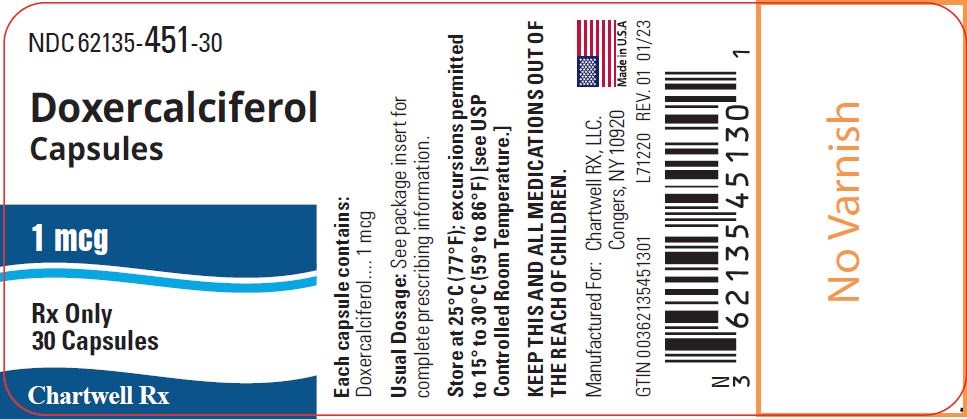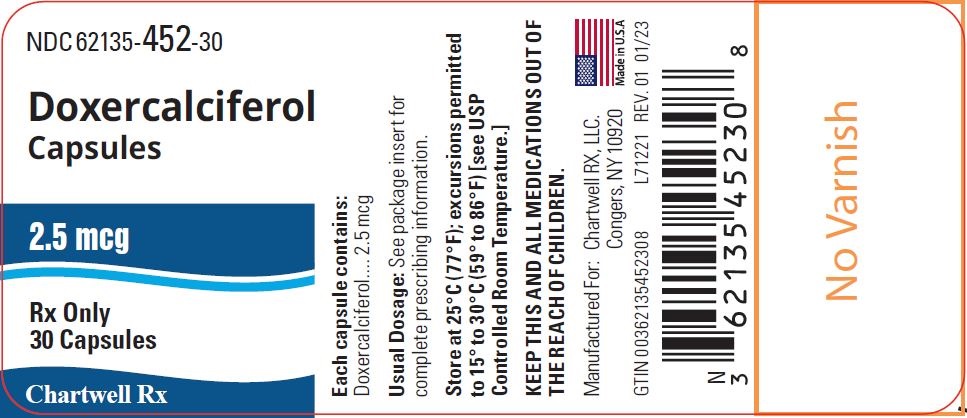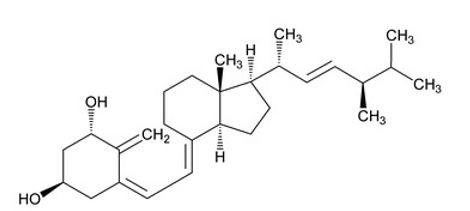 DRUG LABEL: Doxercalciferol
NDC: 62135-450 | Form: CAPSULE
Manufacturer: Chartwell RX, LLC
Category: prescription | Type: HUMAN PRESCRIPTION DRUG LABEL
Date: 20241010

ACTIVE INGREDIENTS: DOXERCALCIFEROL 0.5 ug/1 1
INACTIVE INGREDIENTS: BUTYLATED HYDROXYANISOLE; ALCOHOL; MEDIUM-CHAIN TRIGLYCERIDES; GELATIN; GLYCERIN; FERROSOFERRIC OXIDE; SHELLAC; TITANIUM DIOXIDE

HIGHLIGHTS OF PRESCRIBING INFORMATION

Doxercalciferol capsules, for oral use
These highlights do not include all the information needed to use doxercalciferol capsules safely and effectively. See full prescribing information for doxercalciferol capsules.
Doxercalciferol capsules, for oral use
Initial U.S. Approval: 1999

1 INDICATIONS AND USAGE

Doxercalciferol Capsules is a synthetic vitamin D2 analog:

- Doxercalciferol capsules are indicated for the treatment of secondary hyperparathyroidism in adult patients with Stage 3 or Stage 4 chronic kidney disease (CKD) and adult patients with CKD on dialysis. (1)

2 DOSAGE AND ADMINISTRATION

- Before initiating treatment, ensure serum calcium is not above the upper limit of normal. (2.1)
- Dosage for doxercalciferol capsules in patients with:
  - Stage 3 or 4 CKD: Initiate dosing at 1 mcg orally once daily. Maximum dose is 3.5 mcg once daily. (2.2)
  - CKD on dialysis: Initiate dosing at 10 mcg orally three times weekly at dialysis (no more frequently than every other day). Maximum dose is 20 mcg three times weekly for a total of 60 mcg weekly. (2.3)
- Target the maintenance dose of doxercalciferol to intact parathyroid hormone (PTH) levels within the desired therapeutic range and serum calcium within normal limits. (2)
- See Full Prescribing Information for dose titration, laboratory monitoring, and important administration instructions. (2)

3 DOSAGE FORMS AND STRENGTHS

- Capsules: 0.5 mcg, 1 mcg, and 2.5 mcg (3)

4 CONTRAINDICATIONS

- Hypercalcemia (4)
- Vitamin D toxicity (4)
- Know hypersensitivity to doxercalciferol or any of the inactive ingredients of doxercalciferol capsules (4)

5 WARNINGS AND PRECAUTIONS

- Hypercalcemia: Can occur during treatment with doxercalciferol and can lead to cardiac arrhythmias and seizures. Severe hypercalcemia may require emergency attention. Risk may be increased when used concomitantly with high dose calcium preparations, thiazide diuretics, or vitamin D compounds. Monitor serum calcium prior to initiation and during treatment and adjust dose accordingly. (2, 5.1)
- Digitalis Toxicity: Hypercalcemia increases the risk of digitalis toxicity. In patients using digitalis compounds, monitor serum calcium and patients for signs and symptoms of digitalis toxicity. Increase frequency of monitoring when initiating or adjusting the dose of doxercalciferol. (5.2)
- Serious Hypersensitivity Reactions: Anaphylaxis, with symptoms of angioedema, hypotension, unresponsiveness, chest discomfort, shortness of breath, and cardiopulmonary arrest, has been reported in hemodialysis patients after administration of doxercalciferol. Monitor patients upon treatment initiation for hypersensitivity reactions. Should a reaction occur, discontinue and treat. (5.3)
- Adynamic Bone Disease: May develop and increase risk of fractures if intact PTH levels are suppressed to abnormally low levels. Monitor intact PTH levels to avoid oversuppression and adjust dose if needed. (5.4)

6 ADVERSE REACTIONS

The most common adverse reactions in patients with Stage 3 or 4 CKD (incidence >5%) were infection, urinary tract infection, chest pain, angina pectoris, constipation, dyspepsia, anemia, leucopenia, dehydration, edema, depression, hypertonia, insomnia, asthenia, paresthesia, cough increased, dyspnea, pruritus, sinusitis, and rhinitis. (6.1)

The most common adverse reactions in patients with CKD on dialysis (incidence >5%) were headache, malaise, edema, nausea/vomiting, dyspnea, dizziness, pruritus, and bradycardia. (6.1)

To report SUSPECTED ADVERSE REACTIONS, contact Chartwell RX, LLC. at 1-845-232-1683 or FDA at 1-800-FDA-1088 or www.fda.gov/medwatch.

7 DRUG INTERACTIONS

- Cytochrome P450 inhibitors: Formation of the active doxercalciferol moiety may be hindered and may necessitate dosage adjustment. Monitor intact PTH and serum calcium concentrations closely. (7)
- Enzyme inducers: Formation of the active doxercalciferol moiety may be affected and may necessitate dosage adjustment. Monitor intact PTH and serum calcium concentrations closely. (7)
- Magnesium-containing products: Combined use may cause hypermagnesemia. Monitor serum magnesium concentrations more frequently and adjust dose as needed. (7)
- Cholestyramine: May impair absorption of doxercalciferol capsules. Administer doxercalciferol capsules at least 1 hour before or 4 to 6 hours after taking cholestyramine. (7)
- Mineral oil or other substances that may affect absorption of fat: May impair absorption of doxercalciferol capsules. Administer doxercalciferol capsules at least 1 hour before or 4 to 6 hours after taking substances that may affect absorption.

FULL PRESCRIBING INFORMATION

1 INDICATIONS AND USAGE

- Doxercalciferol capsules are indicated for the treatment of secondary hyperparathyroidism in adult patients with Stage 3 or Stage 4 chronic kidney disease (CKD) and adult patients with CKD on dialysis.

2 DOSAGE AND ADMINISTRATION

2.1 Prior to Initiation of Doxercalciferol Capsules

- Ensure serum calcium is not above the upper limit of normal before initiating treatment with doxercalciferol capsules [see Warnings and Precautions (5.1)].

2.2 Dosage Recommendations for Doxercalciferol Capsules in Patients with Stage 3 or 4 CKD

- Initiate doxercalciferol capsules at a dose of 1 mcg orally once daily.
- Target the maintenance dose of doxercalciferol to intact parathyroid hormone (PTH) levels within the desired therapeutic range and serum calcium within normal limits.
- Monitor serum calcium, phosphorus, and intact PTH levels at least every two weeks for 3 months after initiation of therapy or dose adjustment, then monthly for 3 months, and every 3 months thereafter.
- Titrate the dose of doxercalciferol capsules based on intact PTH. The dose may be increased at 2-week intervals by 0.5 mcg to achieve the desired therapeutic range of intact PTH. The maximum recommended dose of doxercalciferol capsules is 3.5 mcg administered once daily. Prior to raising the dose, ensure serum calcium is within normal limits.
- Suspend or decrease the dose if intact PTH is persistently and abnormally low to reduce the risk of adynamic bone disease [see Warnings and Precautions (5.4)] or if serum calcium is consistently above the normal range to reduce the risk of hypercalcemia [see Warnings and Precautions (5.1)]. If suspended, the drug should be restarted after one week at a dose that is at least 0.5 mcg lower.

2.3 Dosage Recommendations for Doxercalciferol Capsules in Patients with CKD on Dialysis

- Initiate doxercalciferol capsules at a dose of 10 mcg orally administered three times weekly at dialysis (no more frequently than every other day).
- Target the maintenance dose of doxercalciferol to intact parathyroid hormone (PTH) levels within the desired therapeutic range and serum calcium within normal limits.
- Monitor serum calcium, phosphorus, and intact PTH levels frequently (e.g., weekly) after initiation of therapy or dose adjustment.
- Titrate the dose of doxercalciferol capsules based on intact PTH. The dose may be increased at 8-week intervals by 2.5 mcg to achieve the desired therapeutic range of intact PTH. The maximum recommended dose of doxercalciferol is 20 mcg administered three times weekly at dialysis for a total dose of 60 mcg weekly. Prior to raising the dose, ensure serum calcium is within normal limits.
- Suspend or decrease the dose if intact PTH is persistently and abnormally low to reduce the risk of adynamic bone disease [see Warnings and Precautions (5.4)] or if serum calcium is consistently above the normal range to reduce the risk of hypercalcemia [see Warnings and Precautions(5.1)]. If suspended, the drug should be restarted one week later at a dose that is at least 2.5 mcg lower.

2.6 Drug Interactions that May Require Dosage Adjustments of Doxercalciferol

- Increased monitoring of serum calcium and dose adjustment of doxercalciferol may be necessary when given concomitantly with drugs that may increase the risk of hypercalcemia [see Drug Interactions (7)].
- Increased monitoring of both serum calcium and intact PTH as well as dose adjustment of doxercalciferol may be necessary when given concomitantly with cytochrome P450 inhibitors or enzyme inducers [see Drug Interactions (7)].

3 DOSAGE FORMS AND STRENGTHS

- 0.5 mcg – White, opaque, oval shaped soft gelatin capsules. Each capsule is imprinted with "HP 538" in black ink.
- 1 mcg – Beige, opaque, oval shaped soft gelatin capsules. Each capsule is imprinted with "HP 539" in black ink.
- 2.5 mcg – Red, opaque, oval shaped soft gelatin capsules. Each capsule is imprinted with "HP 540" in black ink.

4 CONTRAINDICATIONS

Doxercalciferol is contraindicated in patients with:

- Hypercalcemia [see Warnings and Precautions (5.1)]
- Vitamin D toxicity [see Warnings and Precautions (5.1)]
- Known hypersensitivity to doxercalciferol or any of the inactive ingredients of doxercalciferol capsules; serious hypersensitivity reactions including anaphylaxis and angioedema have been reported [see Warnings and Precautions (5.3), Adverse Reactions (6.2)].

5 WARNINGS AND PRECAUTIONS

5.1 Hypercalcemia

Hypercalcemia may occur during doxercalciferol treatment. Acute hypercalcemia may increase the risk of cardiac arrhythmias and seizures and may potentiate the effect of digitalis on the heart [see Warnings and Precautions (5.2)]. Chronic hypercalcemia can lead to generalized vascular calcification and other soft-tissue calcification. Severe hypercalcemia may require emergency attention.

Hypercalcemia may be exacerbated by concomitant administration of high doses of calcium-containing preparations, thiazide diuretics, or other vitamin D compounds [see Drug Interactions (7)]. In addition, high intake of calcium and phosphate concomitantly with vitamin D compounds may lead to hypercalciuria and hyperphosphatemia. Patients with a history of hypercalcemia prior to initiating therapy may be at increased risk for development of hypercalcemia with doxercalciferol. In these circumstances, frequent serum calcium monitoring and doxercalciferol dose adjustments may be required.

When initiating doxercalciferol or adjusting doxercalciferol dose, measure serum calcium frequently (weekly in patients with CKD on dialysis or every 2 weeks for patients with stage 3 or 4 CKD). Once a maintenance dose has been established, measure serum calcium monthly for 3 months and then every 3 months . If hypercalcemia occurs, reduce the dose or discontinue doxercalciferol until serum calcium is normal [see Dosage and Administration (2)].

Inform patients about the symptoms of elevated calcium (feeling tired, difficulty thinking clearly, loss of appetite, nausea, vomiting, constipation, increased thirst, increased urination and weight loss) and instruct them to report new or worsening symptoms when they occur.

5.2 Digitalis Toxicity

Doxercalciferol can cause hypercalcemia [see Warnings and Precautions (5.1)] which increases the risk of digitalis toxicity. In patients using doxercalciferol concomitantly with digitalis compounds, monitor both serum calcium and patients for signs and symptoms of digitalis toxicity. Increase the frequency of monitoring when initiating or adjusting the dose of doxercalciferol [see Drug Interactions (7)].

5.3 Serious Hypersensitivity Reactions

Hypersensitivity reactions include anaphylaxis with symptoms of angioedema (involving face, lips, tongue and airways), hypotension, unresponsiveness, chest discomfort, shortness of breath, and cardiopulmonary arrest. These reactions may occur separately or together.

Monitor patients receiving doxercalciferol upon initiation of treatment for hypersensitivity reactions. Should a hypersensitivity reaction occur, discontinue doxercalciferol, monitor and treat if indicated [see Contraindications (4)].

5.4 Adynamic Bone Disease

Adynamic bone disease with subsequent increased risk of fractures may develop if intact PTH levels are suppressed by doxercalciferol to abnormally low levels. Monitor intact PTH levels to avoid oversuppression and adjust the doxercalciferol dose, if needed [see Dosage and Administration (2)].

6 ADVERSE REACTIONS

The following adverse reactions are discussed in greater detail in another section of the label:

- Hypercalcemia [see Warnings and Precautions (5.1)]
- Serious Hypersensitivity Reactions [see Warnings and Precautions (5.3)]
- Adynamic Bone Disease [see Warnings and Precautions (5.4)]

6.1 Clinical Trials Experience

Because clinical trials are conducted under widely varying conditions, adverse reaction rates observed in the clinical trials of a drug cannot be directly compared to rates in the clinical trials of another drug and may not reflect the rates observed in practice.

Adverse reactions in patients with stage 3 or 4 CKD

Doxercalciferol capsules have been evaluated in two placebo-controlled, double-blind 24 week studies in patients with Stage 3 or 4 CKD. Patients were treated with doxercalciferol capsules (n=27) or placebo (n=28) [see Clinical Studies (14.1)]. Adverse reactions occurring in the doxercalciferol capsules group at a frequency of 5% or greater and more frequently than in the placebo group are presented in Table 1.

Table 1: Adverse Reactions Occurring in ≥5% Doxercalciferol Capsule-Treated Patients with CKD on Predialysis and Greater than Placebo in Two Double-Blind Clinical Studies
Adverse Reaction [Pooled data on adverse reactions from clinical study reports (Studies BCI-CH-115 and BCI-CH-119).] | Doxercalciferol (n=27) % | Placebo (n=28) %
Infection/bacterial infection/viral infection | 30 | 25
Constipation | 26 | 11
Rhinitis | 22 | 11
Anemia | 19 | 4
Cough | 19 | 4
Dyspnea | 19 | 11
Paresthesia | 15 | 11
Asthenia | 15 | 11
Insomnia | 15 | 4
Hypertonia | 11 | 4
Angina pectoris | 8 | 0
Dehydration | 7 | 4
Depression | 7 | 0
Dyspepsia | 7 | 4
Edema | 7 | 4
Urinary tract infection | 7 | 4
Leukopenia | 7 | 0
Chest pain | 7 | 4
Pruritus | 7 | 4
Sinusitis | 7 | 4

Adverse reactions in patients with CKD on dialysis

Doxercalciferol capsules have been evaluated in two placebo-controlled, double-blind studies in patients with CKD on hemodialysis. Patients were treated with doxercalciferol capsules (n=61) or placebo (n=61) [see Clinical Studies (14.2)]. After randomization to two groups, eligible patients underwent an 8-week washout period during which no vitamin D derivatives were administered to either group. Subsequently, all patients received doxercalciferol capsules in an open-label fashion for 16 weeks followed by a double-blind period of 8 weeks during which patients received either doxercalciferol capsules or placebo. Adverse reactions occurring in the doxercalciferol capsule groups at a frequency of 2% or greater, and more frequently than in the placebo group are presented in Table 2.

Table 2: Adverse Reactions Occurring in ≥2% Doxercalciferol Capsule-Treated Patients with CKD on Dialysis and Greater than Placebo in Two Double-Blind Clinical Studies
Adverse Reaction [A patient who reported the same medical term more than once was counted only once for that medical term.] | Doxercalciferol (n=61) % | Placebo (n=61) %
Edema | 34 | 21
Malaise | 28 | 20
Headache | 28 | 18
Nausea/Vomiting | 21 | 20
Dizziness | 12 | 10
Dyspnea | 12 | 7
Pruritus | 8 | 7
Bradycardia | 7 | 5
Anorexia | 5 | 3
Dyspepsia | 5 | 2
Arthralgia | 5 | 0
Weight increase | 5 | 0
Abscess | 3 | 0
Sleep disorder | 3 | 0

6.2 Postmarketing Experience

The following adverse reactions have been identified during postapproval use of doxercalciferol. Because these reactions are reported voluntarily from a population of uncertain size, it is not always possible to estimate their frequency or to establish a causal relationship to drug exposure.

Hypersensitivity reactions include anaphylaxis with symptoms of angioedema (involving face, lips, tongue and airways), hypotension, unresponsiveness, chest discomfort, shortness of breath, cardiopulmonary arrest, pruritus, and skin burning sensation.

7 DRUG INTERACTIONS

Tables 3 and 4 include clinically significant drug interactions with doxercalciferol.

Table 3: Clinically Significant Drug Interactions with Doxercalciferol Capsules
Drugs that May Increase the Risk of Hypercalcemia
Clinical Impact | Concomitant administration of high doses of calcium-containing preparations or other vitamin D compounds may increase the risk of hypercalcemia. Thiazide diuretics are known to induce hypercalcemia by reducing excretion of calcium in the urine.
Examples | Calcium-containing products, other vitamin D compounds or thiazide diuretics
Intervention | Monitor serum calcium concentrations more frequently and adjust doxercalciferol dose as needed [see Warnings and Precautions (5.1)].
Digitalis Compounds
Clinical Impact | Doxercalciferol can cause hypercalcemia which can potentiate the risk of digitalis toxicity.
Intervention | Monitor patients for signs and symptoms of digitalis toxicity and increase frequency of serum calcium monitoring when initiating or adjusting the dose of doxercalciferol in patients receiving digitalis compounds [see Warnings and Precautions (5.2)].
Cytochrome P450 Inhibitors
Clinical Impact | Doxercalciferol is activated by CYP 27 in the liver. Cytochrome P450 inhibitors may inhibit the 25-hydroxylation of doxercalciferol and thus reduce the formation of active doxercalciferol moiety [see Clinical Pharmacology (12.3)].
Examples | Ketoconazole and erythromycin
Intervention | If a patient initiates or discontinues therapy with a cytochrome P450 inhibitor, dose adjustment of doxercalciferol may be necessary. Monitor intact PTH and serum calcium concentrations closely.
Enzyme Inducers
Clinical Impact | Doxercalciferol is activated by CYP 27 in the liver. Enzyme inducers may affect the 25-hydroxylation of doxercalciferol [see Clinical Pharmacology (12.3)].
Examples | Glutethimide and phenobarbital
Intervention | If a patient initiates or discontinues therapy with an enzyme inducer, dose adjustment of doxercalciferol may be necessary. Monitor intact PTH and serum calcium concentrations closely.
Magnesium-containing Products
Clinical Impact | Concomitant administration of doxercalciferol and high doses of magnesium-containing products may increase the risk of hypermagnesemia.
Examples | Magnesium-containing products such as antacids
Intervention | Avoid use of magnesium-containing products and doxercalciferol in patients on chronic renal dialysis.

Table 4: Clinically Significant Drug Interactions with Doxercalciferol Capsules
Cholestyramine
Clinical Impact | Cholestyramine has been reported to reduce intestinal absorption of fat-soluble vitamins. Therefore, it may impair intestinal absorption of doxercalciferol capsules.
Intervention | Administer doxercalciferol capsules at least 1 hour before or 4 to 6 hours after taking cholestyramine.
Mineral Oil or other Substances that May Affect Absorption of Fat
Clinical Impact | The use of mineral oil or other substances that may affect absorption of fat may influence the absorption and availability of doxercalciferol.
Intervention | Administer doxercalciferol capsules at least 1 hour before or 4 to 6 hours after taking mineral oil or other substances that may affect absorption of fat.

8 USE IN SPECIFIC POPULATIONS

8.1 Pregnancy

Risk Summary

The limited available data with doxercalciferol in pregnant women are insufficient to identify a drug-associated risk for major birth defects, miscarriage or adverse maternal or fetal outcomes. There are risks to the mother and fetus associated with chronic kidney disease in pregnancy [see Clinical Considerations] . In reproduction studies in rats and rabbits administered doxercalciferol during organogenesis at up to 20 mcg/kg/day and 0.1 mcg/kg/day, respectively (approximately 25 times (rats) and less than (rabbits) the maximum recommended human oral dose of 60 mcg/week based on mcg/m^2 body surface area), no adverse developmental effects were observed [see Data] .

The estimated background risk of major birth defects and miscarriage for the indicated population is unknown. In the U.S. general population, the estimated background risk of major birth defects and miscarriage in clinically recognized pregnancies is 2% to 4% and 15% to 20%, respectively.

Clinical Considerations

Disease-associated maternal and/or embryo/fetal risk

Chronic kidney disease in pregnancy increases the risk for maternal hypertension and preeclampsia,

miscarriage, preterm delivery polyhydramnios, stillbirth, and low-birth-weight infants.

Data

Animal data

There were no adverse effects on fetal development when doxercalciferol was administered at doses up to 20 mcg/kg/day in pregnant rats or doses up to 0.1 mcg/kg/day in pregnant rabbits during the period of organogenesis.

8.2 Lactation

Risk Summary

There is no information available on the presence of doxercalciferol in human milk, the effects of the drug on the breastfed infant, or the effects of the drug on milk production. Infants exposed to doxercalciferol through breast milk should be monitored for signs and symptoms of hypercalcemia [see Clinical Considerations] .

The developmental and health benefits of breastfeeding should be considered along with the mother's clinical need for doxercalciferol and any potential adverse effects on the breastfed child from doxercalciferol or from the underlying maternal condition.

Clinical Considerations

Monitoring of serum calcium in the infant should be considered.

8.4 Pediatric Use

Safety and efficacy of doxercalciferol in pediatric patients have not been established.

8.5 Geriatric Use

Clinical studies of doxercalciferol did not include sufficient numbers of patients 65 years or over to determine whether they respond differently from younger subjects. In general, dose selection for an elderly patient should be cautious, usually starting at the low end of the dosing range, reflecting the greater frequency of decreased hepatic or cardiac function, and of concomitant disease or other drug therapy.

8.6 Hepatic Impairment

Patients with hepatic impairment may not metabolize doxercalciferol appropriately. More frequent monitoring of intact PTH, calcium, and phosphorus levels should be done in patients with hepatic impairment.

10 OVERDOSAGE

Overdosage of doxercalciferol may lead to hypercalcemia, hypercalciuria, and hyperphosphatemia [see Warnings and Precautions (5.1)]. The treatment of acute overdosage should consist of supportive measures and discontinuation of doxercalciferol administration. Serum calcium levels should be measured until normal.

Based on similarities between doxercalciferol and its active metabolite, 1α,25-(OH)2D2, it is expected that doxercalciferol is not removed from the blood by dialysis.

11 DESCRIPTION

Doxercalciferol Capsules contains doxercalciferol, which is a synthetic vitamin D2 analog. Doxercalciferol undergoes metabolic activation in vivo to form 1α,25-dihydroxyvitamin D2 (1α,25-(OH)2D2), a naturally occurring, biologically active form of vitamin D2.

Doxercalciferol is a colorless crystalline compound with a calculated molecular weight of 412.66 and a molecular formula of C28H44O2. It is soluble in oils and organic solvents, but is relatively insoluble in water. Chemically, doxercalciferol is (1α,3β,5Z,7E,22E)-9,10-secoergosta-5,7,10(19),22-tetraene-1,3-diol. The structural formula is:

Doxercalciferol capsules are soft gelatin capsules containing 0.5 mcg, 1 mcg, or 2.5 mcg doxercalciferol for oral use. Each capsule also contains butylated hydroxyanisole (BHA), ethanol, and medium-chain triglycerides. The capsule shells contain gelatin, glycerin, iron oxide black and titanium dioxide. In addition, the 0.5 mcg capsule shells contain shellac glaze, the 1 mcg capsule shells contain FD&C Blue No. 1, FD&C Yellow No. 6, shellac and the 2.5 mcg capsule shells contain FD&C Red No. 40 and shellac.

12 CLINICAL PHARMACOLOGY

12.1 Mechanism of Action

Doxercalciferol is a synthetic vitamin D2 analog that requires metabolic activation to form the active 1α,25-(OH)2D2 metabolite, which binds to the vitamin D receptor (VDR) to result in the selective activation of vitamin D responsive pathways. Vitamin D and doxercalciferol have been shown to reduce PTH levels by inhibiting PTH synthesis and secretion.

12.3 Pharmacokinetics

Absorption

In healthy volunteers, peak blood levels of 1α,25-(OH)2D2, the major metabolite of doxercalciferol, are attained at 8 hours after a single intravenous dose of doxercalciferol and at 11 to 12 hours following capsule doses.

Elimination

The mean elimination half-life of 1α,25-(OH)2D2 after an oral dose is approximately 32 to 37 hours with a range of up to 96 hours.

Metabolism

Doxercalciferol is activated by CYP 27 in the liver to form 1α,25-(OH)2D2 (major metabolite) and 1α,24-dihydroxyvitamin D2 (minor metabolite). Activation of doxercalciferol does not require the involvement of the kidneys.

Specific Populations

Patients with renal impairment

The mean elimination half-life of 1α,25-(OH)2D2 in patients with end-stage renal disease (ESRD) and in healthy volunteers appears to be similar following an oral dose. Hemodialysis causes a temporary increase in 1α,25- (OH)2D2 mean concentrations, presumably due to volume contraction. 1α,25-(OH)2D2 is not removed from blood during hemodialysis.

13 NONCLINICAL TOXICOLOGY

13.1 Carcinogenesis, Mutagenesis, Impairment of Fertility

In a 104-week carcinogenicity study in rats, there was an increased incidence of benign and malignant adrenal pheochromocytomas in both males and females at oral doses of 0.04, 0.13, and 0.39 mcg/kg/day (less than the maximum recommended human oral dose of 60 mcg/week based on mcg/m^2 body surface area). This increased incidence of pheochromocytomas in rats may be due to altered calcium homeostasis by doxercalciferol. No evidence of genetic toxicity was observed in an in vitro bacterial mutagenicity assay (Ames test) or a mouse lymphoma gene mutation assay. Doxercalciferol caused structural chromatid and chromosome aberrations in an in vitro human lymphocyte clastogenicity assay with metabolic activation. However, doxercalciferol was negative in an in vivo mouse micronucleus clastogenicity assay.

Doxercalciferol had no effect on male or female fertility in rats at oral doses up to 2.5 mcg/kg/day (approximately 3 times the maximum recommended human oral dose of 60 mcg/week based on mcg/m^2 body surface area).

14 CLINICAL STUDIES

14.1 Clinical Studies of Doxercalciferol Capsules in Patients with Stage 3 or 4 CKD

The safety and effectiveness of doxercalciferol capsules were evaluated in two clinical studies in 55 patients with Stage 3 or 4 CKD. Eighty-two percent of the patients were male, the average age was 65 years, 51% were Caucasian, 40% African-American, and the average serum intact PTH level at baseline was 195 pg/mL. While levels of 25-(OH) vitamin D were not evaluated at baseline, retrospective assessments of stored serum revealed that the mean ± SD serum 25-(OH) vitamin D was 19 ± 8 ng/mL (range: <5 to 54 ng/mL) in the study population.

After randomization to two groups, eligible patients underwent an 8-week washout period during which no vitamin D derivatives were administered to either group. Subsequently, one group received doxercalciferol capsules and the other placebo during the double-blind period of 24 weeks. The initial dose of doxercalciferol capsules was 1 mcg per day. The dosage of doxercalciferol capsules was adjusted as necessary by the investigator to reduce intact PTH levels to a target of ≥30% below post-washout baseline. The maximum dosage was limited to 3.5 mcg per day. If at any time during the trial intact PTH fell below 15 pg/mL, doxercalciferol capsules were immediately suspended and restarted at a lower dosage the following week.

Decreases in the mean plasma intact PTH from baseline values were calculated using as baseline the average of the last 2 values obtained during the 8-week washout phase. In analyses of pooled data from the two studies, intact PTH levels decreased from baseline by an average of 101 pg/mL in the doxercalciferol capsules group and by 4 pg/mL in the placebo group (p<0.001). Twenty (74%) of 27 subjects in the doxercalciferol capsules group achieved mean plasma intact PTH suppression of ≥30% from baseline for the last four weeks of treatment, whereas two (7%) of the 28 subjects treated with placebo achieved this level of intact PTH suppression.

14.2 Clinical Studies of Doxercalciferol Capsules in Patients with CKD on Dialysis

The safety and effectiveness of doxercalciferol capsules were evaluated in two double-blind, placebo-controlled, multicenter clinical studies (Study A and Study B) in a total of 138 patients with CKD on hemodialysis. Patients in Study A were an average age of 52 years (range: 22 to 75), were 55% male, and were 58% African-American, 31% Caucasian, and 11% Hispanic, and had been on hemodialysis for an average of 53 months. Patients in Study B were an average of 52 years (range: 27 to 75), were 45% male, and 99% African-American, and 1% Caucasian, and had been on hemodialysis for an average of 56 months. After randomization to two groups, eligible patients underwent an 8-week washout period during which no vitamin D derivatives were administered to either group. Subsequently, all patients received doxercalciferol capsules in an open-label fashion for 16 weeks followed by a double-blind period of 8 weeks during which patients received either doxercalciferol capsules or placebo. The initial dose of doxercalciferol capsules during the open-label phase was 10 mcg after each dialysis session (3 times weekly) for a total of 30 mcg per week. The dosage of doxercalciferol was adjusted as necessary by the investigator to achieve intact PTH levels within 150 pg/mL to 300 pg/mL. The maximum dosage was limited to 20 mcg after each dialysis session (60 mcg/week). If at any time during the trial intact PTH fell below 150 pg/mL, Doxercalciferol was immediately suspended and restarted at a lower dosage the following week. Mean weekly doses during the 16-week open-label period ranged from 15 mcg to 29 mcg in Study A and from 19 mcg to 28 mcg in Study B.

One hundred and six (77%) of the 138 patients who were treated with doxercalciferol capsules during the 16- week open-label phase achieved intact PTH levels ≤300 pg/mL. Ninety-four (68%) of these patients exhibited plasma intact PTH levels ≤300 pg/mL on at least 3 occasions. Eighty-seven (63%) patients had plasma intact PTH levels <150 pg/mL on at least one occasion during the open-label phase of study participation.

Decreases in plasma intact PTH from baseline values were calculated using as baseline the average of the last 3 values obtained during the 8-week washout phase and are displayed in Table 5.

Table 5: Intact PTH Summary Data for Patients with CKD on Dialysis Receiving Doxercalciferol Capsules in Studies A and B
 |  | Intact PTH (pg/mL)
 |  | means ± SD (n)* p-value vs Baseline p-value vs Placebo
 |  | Doxercalciferol Capsules | Placebo
Study A | Baseline | 797.2 ± 443.8 (30) NA 0.97 | 847.1 ± 765.5 (32) – –
Study A | Week 16 (open-label) | 384.3 ± 397.8 (24) <0.001 0.72 | 526.5 ± 872.2 (29) <0.001 –
Study A | Week 24 (double-blind) | 404.4 ± 262.9 (21) <0.001 0.008 | 672.6 ± 356.9 (24) 0.70 –
Study B | Baseline | 973.9 ± 567.0 (41) NA 0.81 | 990.4 ± 488.3 (35) – –
Study B | Week 16 (open-label) | 476.1 ± 444.5 (37) <0.001 0.91 | 485.9 ± 443.4 (32) <0.001 –
Study B | Week 24 (double-blind) | 459.8 ± 443.0 (35) <0.001 <0.001 | 871.9 ± 623.6 (30) <0.065 –
* All subjects; last value carried to discontinuation.
NA = not applicable

Doxercalciferol capsules treatment resulted in a statistically significant reduction from baseline in mean intact PTH levels during the 16-week open-label treatment period in more than 94% of the 138 treated patients. During the double-blind period (weeks 17 to 24), the reduction in mean intact PTH levels was maintained in the doxercalciferol capsules treatment group compared to a return to near baseline in the placebo group.

16 HOW SUPPLIED/STORAGE AND HANDLING

How Supplied

Doxercalciferol capsules are oval, soft gelatin capsules supplied as follows.

Strength | Capsule Color | Imprint Code | Package Size | NDC
0.5 mcg | White, Opaque | HP 538 | Bottle of 30 capsules | 62135-450-30
1 mcg | Beige, Opaque | HP 539 | Bottle of 30 capsules | 62135-451-30
2.5 mcg | Red, Opaque | HP 540 | Bottle of 30 capsules | 62135-452-30

Storage and Handling

Store at 25°C (77°F); excursions permitted to 15° to 30°C (59° to 86°F)

[see USP Controlled Room Temperature.]

17 PATIENT COUNSELING INFORMATION

Hypercalcemia

Advise patients to contact a health care provider if they develop symptoms of elevated calcium (e.g. feeling tired, difficulty thinking clearly, loss of appetite, nausea, vomiting, constipation, increased thirst, increased urination and weight loss) [see Warnings and Precautions (5.1)] .

Hypersensitivity

Inform patients that hypersensitivity reactions can occur with doxercalciferol [see Warnings and Precautions (5.3)].

Monitoring

Inform patients that they will need routine monitoring of laboratory parameters such as calcium and intact PTH while receiving doxercalciferol. Inform patients that more frequent monitoring is necessary during the initiation of therapy, following dose changes or when potentially interacting medications are started or discontinued [see Dosage and Administration (2), Drug Interactions (7)] .

Drug Interactions

Advise patients to inform their physician of all medications, including prescription and nonprescription drugs, and supplements they are taking. Advise patients to also inform their physician that they are receiving doxercalciferol if a new medication is prescribed [see Drug Interactions (7)].

Manufactured for:
Chartwell RX, LLC.

Congers, NY 10920

L71222

Revised 01/2023

PACKAGE LABEL.PRINCIPAL DISPLAY PANEL

Doxercalciferol Capsules 0.5mcg-NDC-62135-450-30-30s-Bottle-Label

Doxercalciferol Capsules 1mcg-NDC-62135-451-30-30s-Bottle-Label

Doxercalciferol Capsules 2.5mcg-NDC-62135-452-30-30s-Bottle-Label